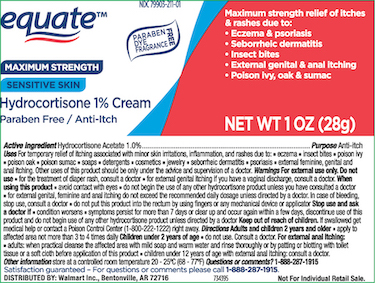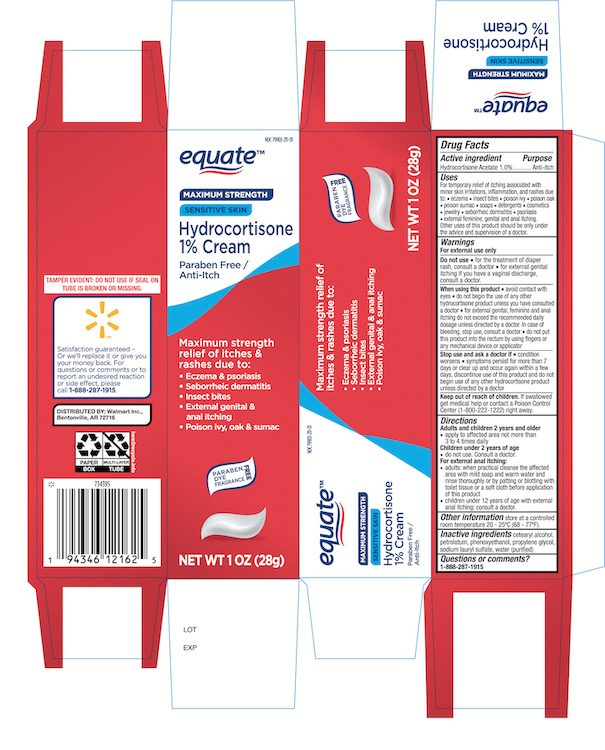 DRUG LABEL: Equate Hydrocortione
NDC: 79903-211 | Form: CREAM
Manufacturer: Walmart Inc.
Category: otc | Type: HUMAN OTC DRUG LABEL
Date: 20260119

ACTIVE INGREDIENTS: HYDROCORTISONE ACETATE 10 mg/1 g
INACTIVE INGREDIENTS: CETOSTEARYL ALCOHOL; PETROLATUM; PHENOXYETHANOL; PROPYLENE GLYCOL; SODIUM LAURYL SULFATE; WATER

Equate Hydrocortisone Cream

Active Ingredient

Hydrocortisone Acetate 1%

Purpose

Anti itch

Uses

For temporarily relief of itching associated with minor skin irritations, inflammation, and rashes due to:

■ eczema ■ psoriasis ■ poison ivy, oak, sumac ■ insect bites ■ detergents ■ jewelry ■ cosmetics

■ soaps ■ seborrheic dermatitis

Other uses of this product should only be under the advice and supervision of a doctor

Do not use

- for the treatment of diaper rash. Consult a doctor.
- for external genital itching if you have a vaginal discharge, consult a doctor.

When using this product

- Avoid contact with the eyes
- Do not begin the use of any other hydrocortisone products unless you have consulted a doctor.
- For genital, feminine and anal itching do not exceed the recommended daily dose unless directed by a doctor, in case of bleeding , stop use and consult a doctor
- Do not put this product into the rectum by using fingers or any mechanical device or applicator.

Stop use and ask a doctor if

condition worsens, symptoms persist for more than 7 days or clear up and occur again within a few days, and do not begin use of any other hydrocortisone product unless you have asked a doctor

Keep out of the reach of children

If swallowed get medical help or contact a poison control center (1-800-222-1222) right away.

Directions

- adults and children 2 years of age and older:apply to affected area not more than 3 to 4 times daily
- children under 2 years of age:do not use, ask a doctor
- For external anal itching ; adults ;when practical cleanse the affected area with mild soap and warm water and rinse thoroughly or by patting or blotting with toilet tissue or a soft cloth before application of this product.Children under 12 years of age with external anal itching consult a doctor.

Other information

store at a controlled room temperature 20-25°C (68-77 F)

Inactive ingredients

Cetearyl Alcohol, Petrolatum, Phenoxyethanol, Propylene Glycol, Sodium Lauryl Sulfate, Water (purified)

Principal Display Panel 1 oz

Equate NDC 79903-211-01

Maximum Strength

Hydrocortisone Cream 1%

Paraben free/Anti-itch

NETWT 1 OZ (28g)